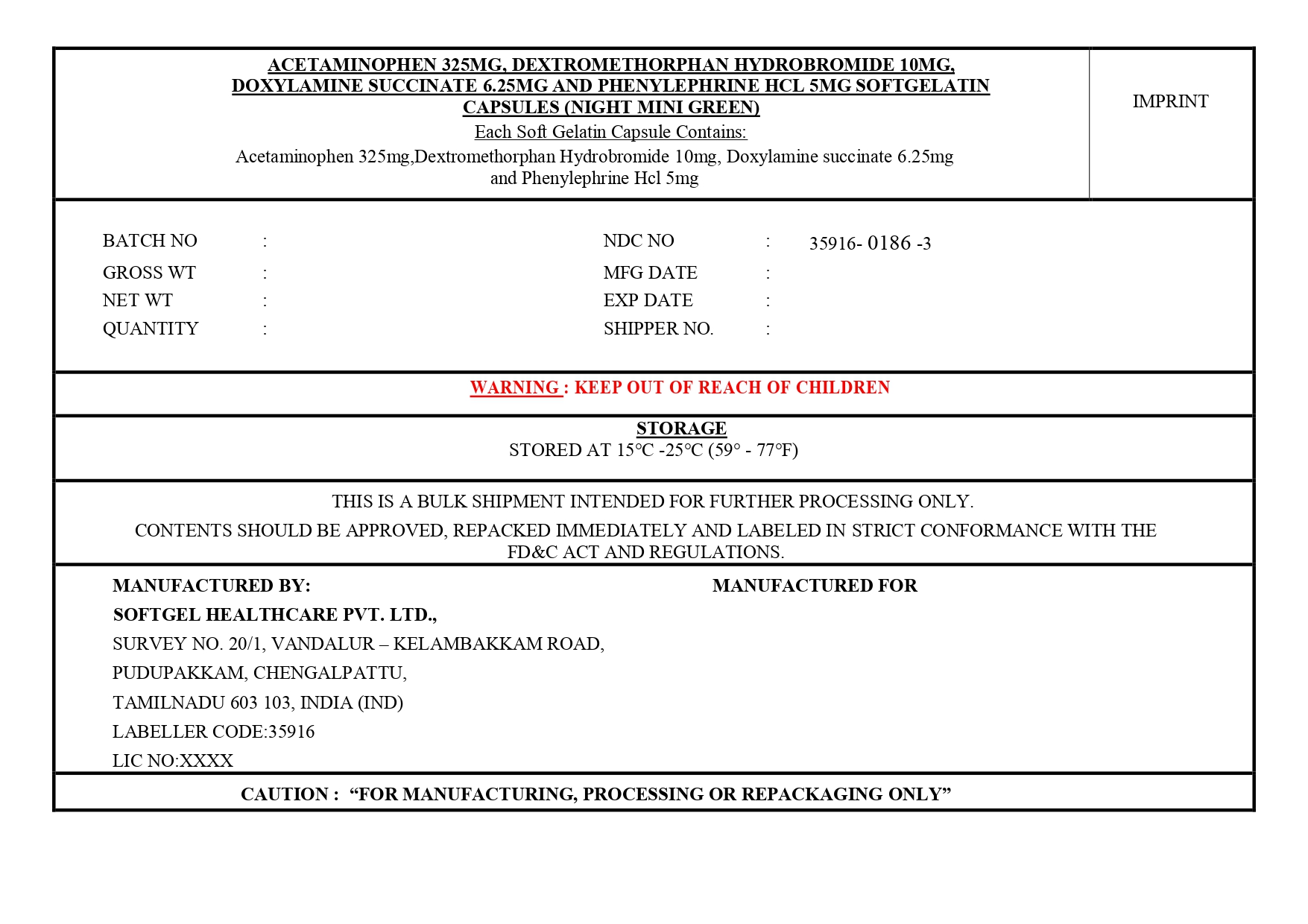 DRUG LABEL: Acetaminophen, Dextromethorphan Hydrobromide, Doxylamine Succinate and Phenylephrine Hydrochloride
NDC: 35916-0186 | Form: CAPSULE, LIQUID FILLED
Manufacturer: Softgel Healthcare Pvt Ltd
Category: otc | Type: HUMAN OTC DRUG LABEL
Date: 20260112

ACTIVE INGREDIENTS: ACETAMINOPHEN 325 mg/1 1; DEXTROMETHORPHAN HYDROBROMIDE 10 mg/1 1; PHENYLEPHRINE HYDROCHLORIDE 5 mg/1 1; DOXYLAMINE SUCCINATE 6.25 mg/1 1
INACTIVE INGREDIENTS: TITANIUM DIOXIDE; MICA; WATER; D&C YELLOW NO. 10; GLYCERIN; GELATIN; FD&C BLUE NO. 1; POLYETHYLENE GLYCOL 400; POVIDONE K30; SORBITOL

Acetaminophen 325 mg , Dextromethorphan Hydrobromide 10 mg, Doxylamine Succinate 6.25 mg and Phenylephrine Hydrochloride 5 mg (Night Mini Green)

Active ingredients (in each Capsule)

Acetaminophen USP 325 mg

Dextromethorphan Hydrobromide USP 10 mg

Doxylamine Succinate USP 6.25 mg

Phenylephrine Hydrochloride USP 5 mg

Purposes

Pain reliever/fever reducer

Cough suppressant

Antihistamine

Nasal decongestant

Uses

temporarily relieves these symptoms due to cold/flu:

- minor aches and pains
- headache
- nasal and sinus congestion
- cough
- sore throat
- runny nose
- sneezing
- temporarily reduces fever

Warnings

Liver warning: This product contains acetaminophen. Severe liver damage may occur if you take

- more than 4,000 mg of acetaminophen in 24 hours
- with other drugs containing acetaminophen
- 3 or more alcoholic drinks every day while using this product

Allergy alert: Acetaminophen may cause severe skin reactions. Symptoms may include:

- Skin reddening
- blisters
- rash
- hives
- facial swelling
- asthma(wheezing)
- shock

If a skin or general allergic reaction occurs, stop use and seek medical help right away.

Sore throat warning: If sore throat is severe, persists for more than 2 days, is accompanied or followed by fever, headache, rash, nausea, or vomiting, consult a doctor promptly.

Do not use to sedate children.

Do not use

- with any other drug containing acetaminophen (prescription or nonprescription). If you are not sure whether a drug contains acetaminophen, ask a doctor or pharmacist.
- if you are now taking a prescription monoamine oxidase inhibitor (MAOI) (certain drugs for depression, psychiatric or emotional conditions, or Parkinson's disease), or for 2 weeks after stopping the MAOI drug. If you do not know if your prescription drug contains an MAOI, ask a doctor or pharmacist before taking this product.
- if you have ever had an allergic reaction to this product or any of its ingredients
- in children under 12 years of age

Ask a doctor before use if you have

- liver disease
- heart disease
- high blood pressure
- thyroid disease
- diabetes
- glaucoma
- cough with excessive phlegm (mucus)
- a breathing problem such as emphysema or chronic bronchitis
- difficulty in urination due to enlaragement of the prostate gland
- persistent or chronic cough such as occurs with smoking,asthma, or emphysema

Ask a doctor or pharmacist before use if you are

- taking the blood thinning drug warfarin
- taking sedatives or tranquilizers

When using this product

- do not exceed recommended dosage
- may cause marked drowsiness
- avoid alcoholic drinks
- alcohol, sedatives, and tranquilizers may increase drowsiness
- be careful when driving a motor vehicle or operating machinery
- excitability may occur, especially in children

Stop use and ask a doctor if

- pain, cough,or nasal congestion gets worse or lasts more than 7 days
- fever gets worse or lasts more than 3 days
- redness or swelling is present
- new symptoms occur
- cough comes back or occurs with rash or headache that lasts.

These could be signs of a serious condition.

- nervousness, dizziness, or sleeplessness occurs

PREGNANCY OR BREAST FEEDING

If pregnant or breast-feeding, ask a health professional before use.

Keep out of reach of children. In case of overdose,get medical help or contact a Poison control center right away. Quick medical medical attention is critical for adults as well as for children even if you do not notice any signs or symptoms.

Directions

- do not take more than the recommended dose
- adults and children 12 years and over: take 2 capsules with water every 4 hours. Do not exceed 4 capsules in 12 hours or as

directed by a doctor.

- children under 12 years: do not use

Other information

Store at 15ºC- 25ºC (59º-77ºF)

Inactive ingredients

candurin silver sheen, candurin silver sparkle, D&C yellow no.10, FD&C blue no.1, gelatin, glycerin, polyethylene glycol 400, povidone K 30, purified water, sorbitol sorbitan solution